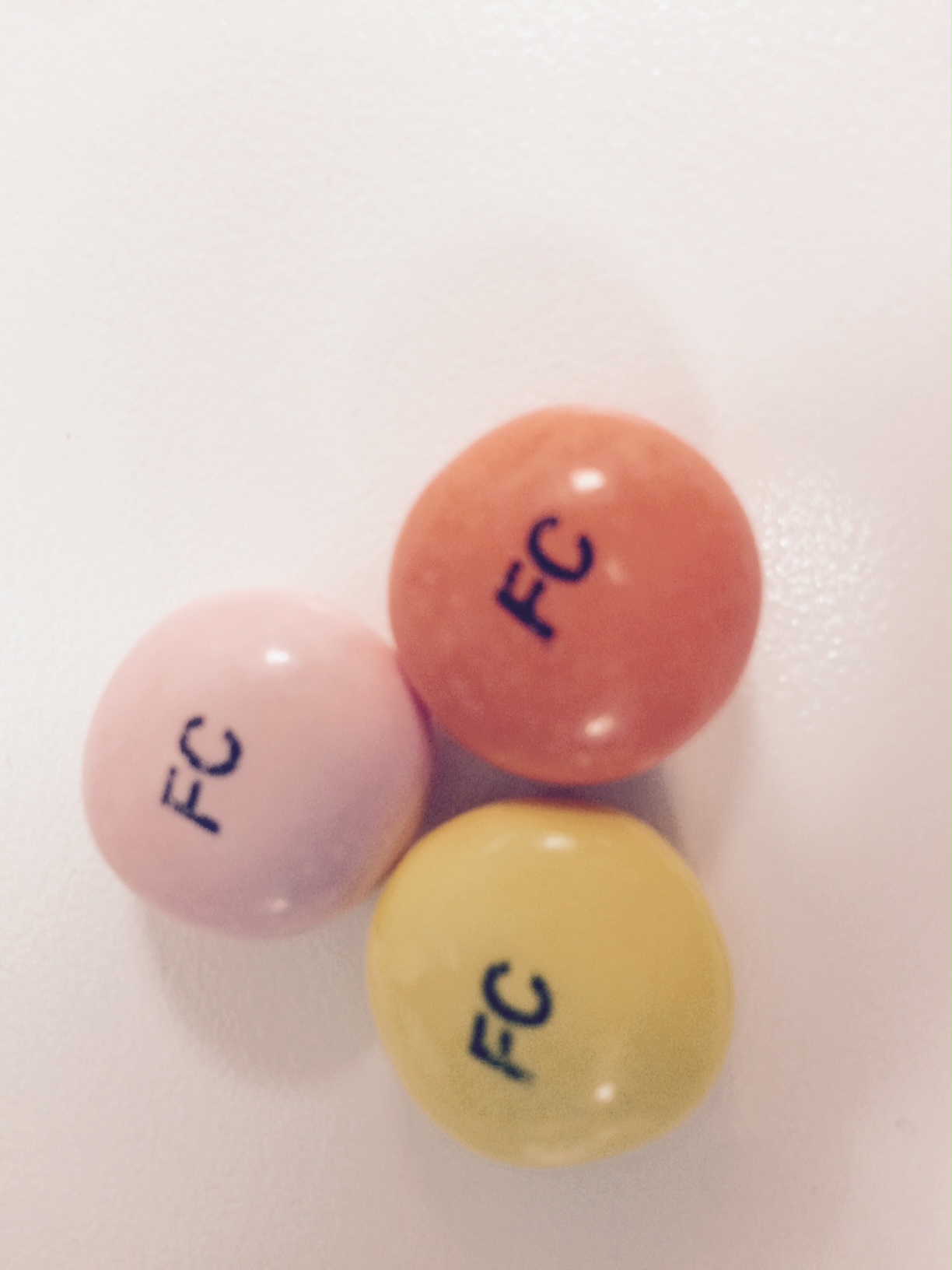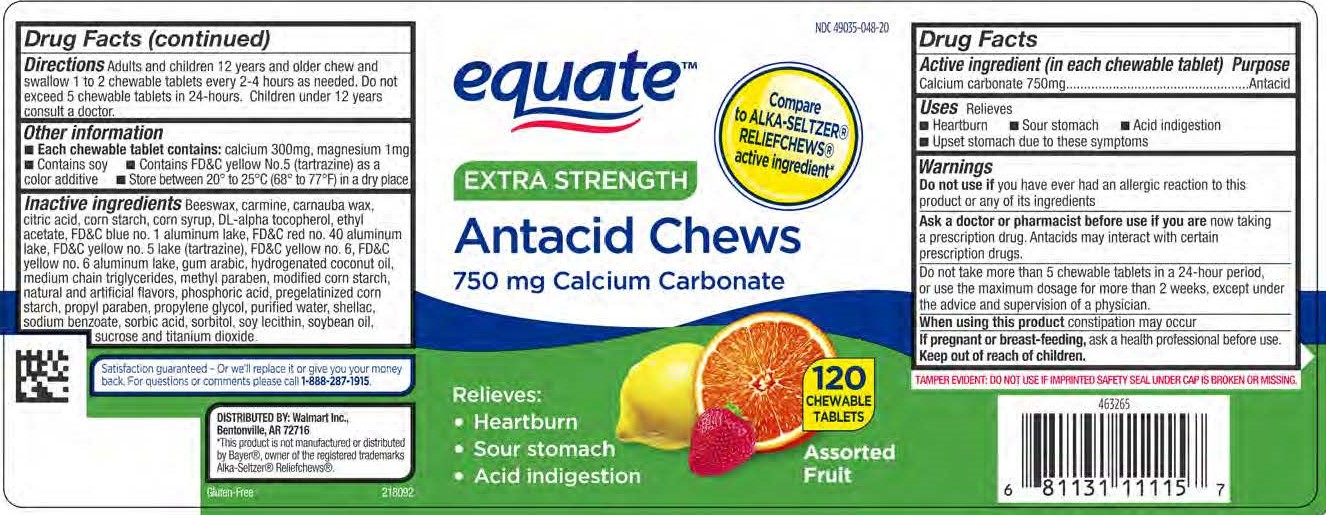 DRUG LABEL: Assorted Fruit Antacid Flavor Chews
NDC: 49035-048 | Form: TABLET, CHEWABLE
Manufacturer: Walmart
Category: otc | Type: HUMAN OTC DRUG LABEL
Date: 20260120

ACTIVE INGREDIENTS: CALCIUM CARBONATE 750 mg/1 1
INACTIVE INGREDIENTS: SUCROSE

Calcium Carbonate 750 mg

Active ingredient (in each chew)

Calcium carbonate 750 mg

Purpose

Antacid

INDICATIONS AND USAGE

Uses: Relieves

- Heartburn
- Sour stomach
- Acid indigestion
- Upset stomach due to these symptoms

Warnings

Do not use if you have ever had an allergic reaction to this product or any of its ingredients

Ask a doctor or pharmacist before use if you are now taking a prescription drug. Antacids may interact with certain prescription drugs.

When using this product do not take more than 5 chewable tablets in a 24-hour period, or use the maximum dosage for more than 2 weeks, except under the advice and supervision of a physician.

When using this product constipation may occur.

PREGNANCY OR BREAST FEEDING

If pregnant or breast-feeding, ask a health professional before use.

Keep out of reach of children.

Directions

Adults and children 12 years and older chew and swallow 1 to 2 chews every 2-4 hours as needed. Do not exceed 5 chews in 24 hours.

Children under 12 years consult a doctor.

Other information

- Each chewable tablet contains: calcium 300 mg, magnesium 1 mg
- Contains soy
- Contains FD&C Yellow No. 5 (tartrazine) as a color additive
- Store between 20° to 25°C (68° to 77°F) in a dry place

Inactive ingredients

Beeswax, carmine, carnauba wax, citric acid, corn starch, corn syrup, DL-alpha tocopherol, ethyl acetate, FD&C blue no. 1 aluminum lake, FD&C red no. 40 aluminum lake, FD&C yellow no. 5 lake (tartrazine), FD&C yellow no. 6, FD&C yellow no. 6 aluminum lake, gum arabic, hydrogenated coconut oil, medium chain triglycerides, methyl paraben, modified corn starch, natural and artificial flavors, phosphoric acid, pregelatinized corn starch, propyl paraben, propylene glycol, purified water, shellac, sodium benzoate, sorbic acid, sorbitol, soy lecithin, soybean oil, sucrose, and titanium dioxide.

Questions? Call 1-888-287-1915